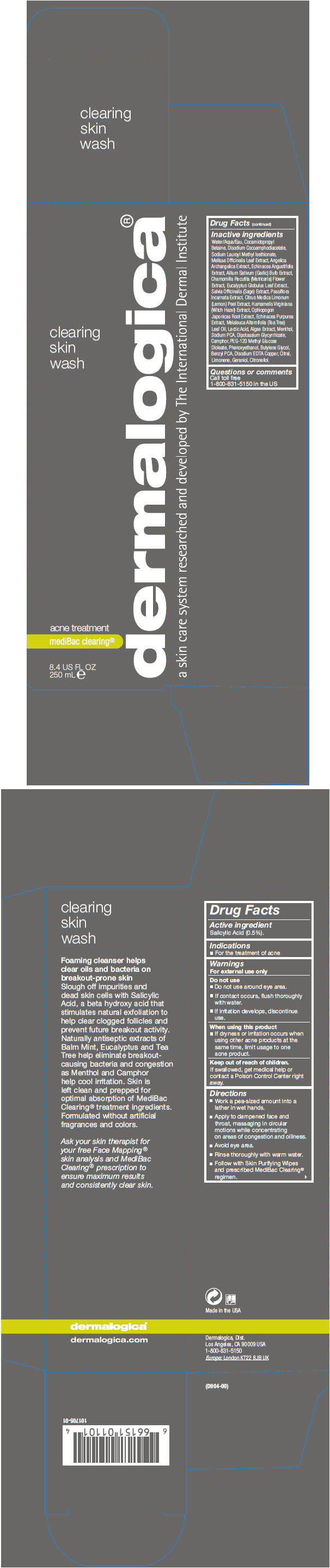 DRUG LABEL: Clearing Skin Wash
NDC: 68479-040 | Form: LIQUID
Manufacturer: Dermalogica, Inc.
Category: otc | Type: HUMAN OTC DRUG LABEL
Date: 20151119

ACTIVE INGREDIENTS: Salicylic Acid 5 mg/1 mL
INACTIVE INGREDIENTS: Water; Cocamidopropyl Betaine; Disodium Cocoamphodiacetate; Sodium Lauroyl Methyl Isethionate; Melissa Officinalis Leaf; Angelica Archangelica Root; Echinacea Angustifolia; Garlic; Chamomile; Eucalyptus Globulus Leaf; Salvia Officinalis Root; Lemon Peel; Hamamelis Virginiana Top; Ophiopogon Japonicus Root; Echinacea Purpurea; Tea Tree Oil; Lactic Acid; Menthol, Unspecified Form; Sodium Pyrrolidone Carboxylate; Glycyrrhizinate Dipotassium; Camphor (Synthetic); PEG-120 Methyl Glucose Dioleate; Phenoxyethanol; Butylene Glycol; Benzyl PCA; Disodium EDTA-Copper

Clearing Skin Wash

Drug Facts

Active ingredient

Salicylic Acid (0.5%).

PURPOSE

Indications

- For the treatment of acne

Warnings

For external use only

- Do not use around eye area.
- If contact occurs, flush thoroughly with water.
- If irritation develops, discontinue use.

When using this product

- If dryness or irritation occurs when using other acne products at the same time, limit usage to one acne product.

Keep out of reach of children.

If swallowed, get medical help or contact a Poison Control Center right away.

Directions

- Work a pea-sized amount into a lather in wet hands.
- Apply to dampened face and throat, massaging in circular motions while concentrating on areas of congestion and oiliness.
- Avoid eye area.
- Rinse thoroughly with warm water.
- Follow with Skin Purifying Wipes and prescribed MediBac Clearing® regimen.

Inactive ingredients

Water/Aqua/Eau, Cocamidopropyl Betaine, Disodium Cocoamphodiacetate, Sodium Lauroyl Methyl Isethionate, Melissa Officinalis Leaf Extract, Angelica Archangelica Extract, Echinacea Angustifolia Extract, Allium Sativum (Garlic) Bulb Extract, Chamomilla Recutita (Matricaria) Flower Extract, Eucalyptus Globulus Leaf Extract, Salvia Officinalis (Sage) Extract, Passiflora Incarnata Extract, Citrus Medica Limonum (Lemon) Peel Extract, Hamamelis Virginiana (Witch Hazel) Extract, Ophiopogon Japonicas Root Extract, Echinacea Purpurea Extract, Melaleuca Alternifolia (Tea Tree) Leaf Oil, Lactic Acid, Algae Extract, Menthol, Sodium PCA, Dipotassium Glycyrrhizate, Camphor, PEG-120 Methyl Glucose Dioleate, Phenoxyethanol, Butylene Glycol, Benzyl PCA, Disodium EDTA Copper, Citral, Limonene, Geraniol, Citronellol.

Questions or comments

Call toll free 1-800-831-5150 in the US

PRINCIPAL DISPLAY PANEL - 250 mL Bottle Carton

clearing
skin
wash

acne treatment

mediBac clearing®

8.4 US FL OZ
250 mL e

dermalogica®